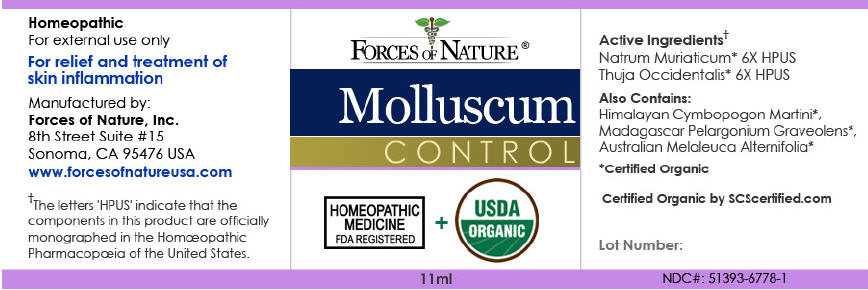 DRUG LABEL: Molluscum Control
NDC: 51393-6778 | Form: SOLUTION/ DROPS
Manufacturer: Forces of Nature
Category: homeopathic | Type: HUMAN OTC DRUG LABEL
Date: 20110331

ACTIVE INGREDIENTS: Thuja Occidentalis Leafy Twig 6 [hp_X]/1000 mL; Sodium Chloride 6 [hp_X]/1000 mL
INACTIVE INGREDIENTS: Tea Tree Oil; Geranium Oil, Algerian Type; Palmarosa Oil

Molluscum Control

Drug Facts

ACTIVE INGREDIENT

PURPOSE

Active Ingredients [The letters 'HPUS' indicate that the component(s) in this product is (are) officially monographed in the Homœopathic Pharmacopœia of the United States.] Equal parts of: | Purpose
Natrum Muriaticum 6X HPUS | Relief for Molluscum, skin conditions and inflammation
Thuja occidentals 6X HPUS | Remedy for skin irritations that itch or burn

Also Includes

Certified Organic oils of: Palmarosa, Pelargonium Graveolens Leaf, Tea Tree

Directions

Apply directly to infected area 3 times per day. For more sensitive skin, apply product to a Q-tip or cotton swab and dab to area. For external use only. Avoid contact to eyes. Discontinue use if continued skin irritation occurs.

Indications

For the relief and treatment of skin inflammation, itching, irritation and redness of molluscum after diagnosis by a physician.

Warnings

This product does not prevent the spread of molluscum.

ASK DOCTOR

If skin symptoms worsen consult a health care professional.

PREGNANCY OR BREAST FEEDING

As with all medication, if you are pregnant or breast-feeding, ask a health professional before use.

KEEP OUT OF REACH OF CHILDREN

Keep out of the reach of children. If accidental ingestion, get medical help or contact a Poison Control Center.

WHEN USING

For external use only. Do not apply to the eyes or mucous membranes.

KEEP OUT OF REACH OF CHILDREN

Keep all medicines out of the reach of children.

PRINCIPAL DISPLAY PANEL - 11ml Bottle Label

FORCES OF NATURE ®

Molluscum
CONTROL

HOMEOPATHIC
MEDICINE
FDA REGISTERED
+
USDA
ORGANIC

11ml